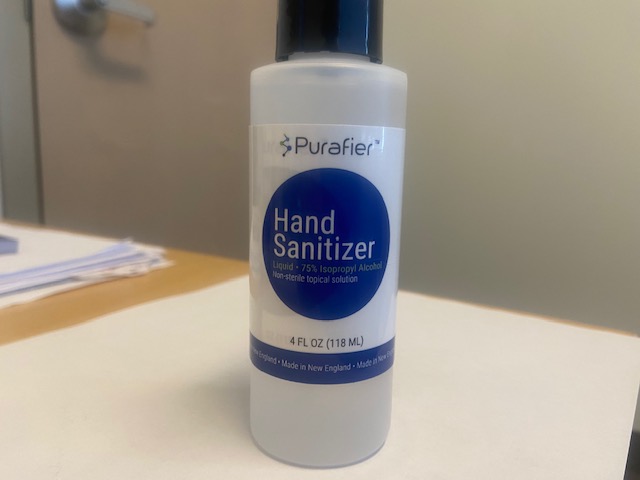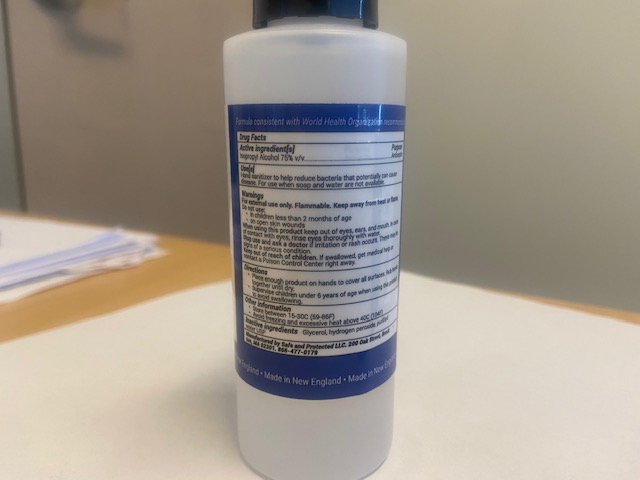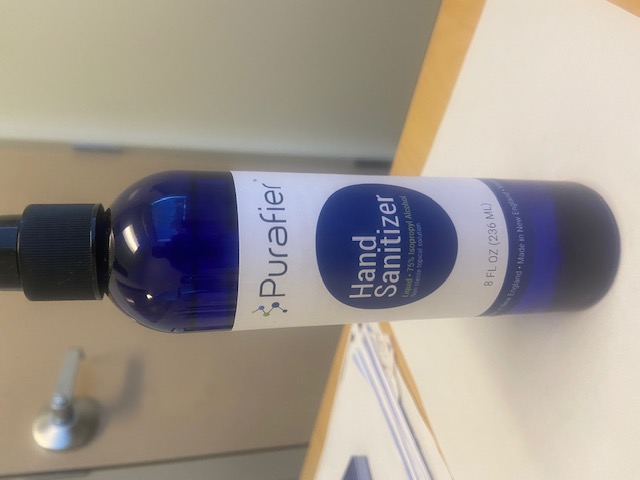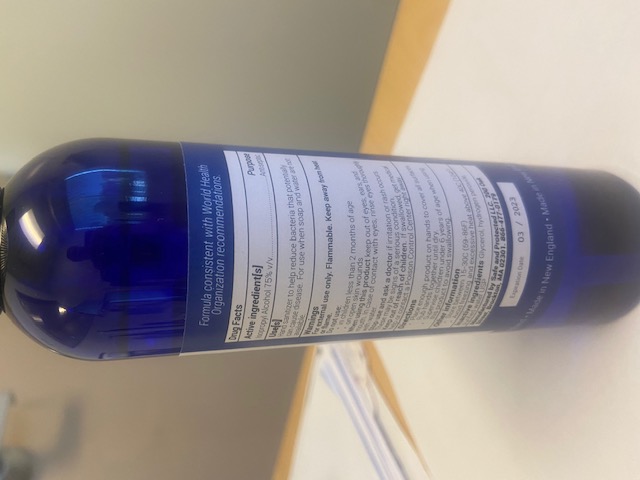 DRUG LABEL: Hand Sanitizer
NDC: 77864-2020 | Form: LIQUID
Manufacturer: Safe and Protected LLC
Category: otc | Type: HUMAN OTC DRUG LABEL
Date: 20201207

ACTIVE INGREDIENTS: ISOPROPYL ALCOHOL 0.75 mL/1 mL
INACTIVE INGREDIENTS: GLYCERIN 0.145 mL/1 mL; HYDROGEN PEROXIDE 0.125 mL/1 mL; WATER

Hand Sanitizer

ACTIVE INGREDIENT

Isopropyl Alcohol 75% - IMG 0322.jpg

Dosage $ Administration Section

Dosage & Administration Sections

Front and Back Label

Principal Display Panel (Front of Package) - IMG 0322.jpg

Drug Facts Label (Back of Package) - IMG 0323.jpg